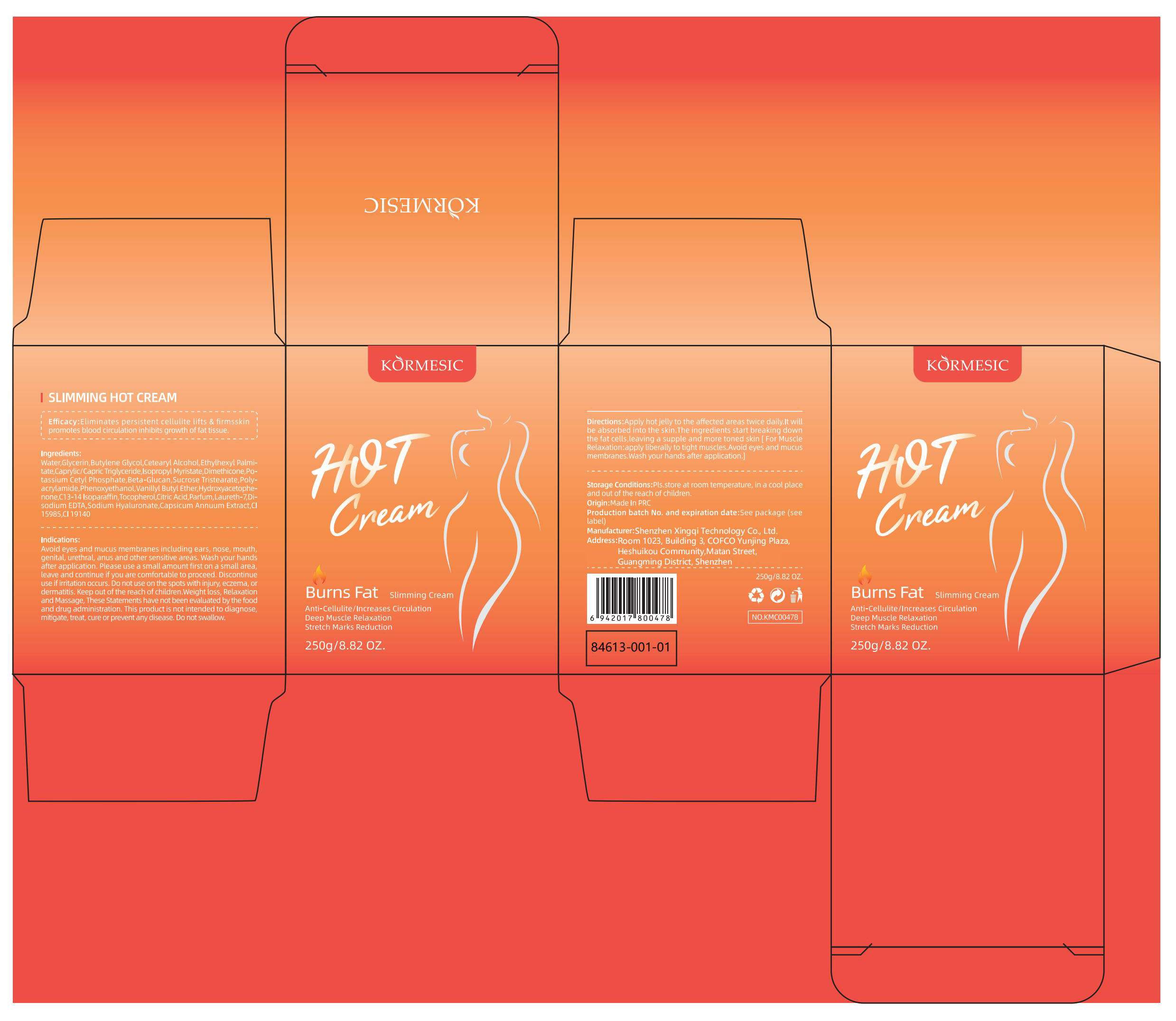 DRUG LABEL: KORMESIC Slimming Hot Cream
NDC: 84613-088 | Form: EMULSION
Manufacturer: Shenzhen Xingqi Technology Co., Ltd.
Category: otc | Type: HUMAN OTC DRUG LABEL
Date: 20240802

ACTIVE INGREDIENTS: HYALURONATE SODIUM 1 g/100 g
INACTIVE INGREDIENTS: BUTYLENE GLYCOL; TRANSFORMING GROWTH FACTOR BETA RECEPTOR TYPE 3; PHENOXYETHANOL; HYDROXYACETOPHENONE; C13-14 ISOPARAFFIN; FRAGRANCE LEMON ORC2001060; WATER; ISOPROPYL MYRISTATE; FD&C YELLOW NO. 5; ETHYLHEXYL PALMITATE; DIMETHICONE; SUCROSE TRISTEARATE; POLYACRYLAMIDE (1500 MW); VANILLYL BUTYL ETHER; TOCOPHEROL; ACONITIC ACID; MEDIUM-CHAIN TRIGLYCERIDES; FD&C YELLOW NO. 6; LAURETH-7; CAPSICUM; GLYCERIN; POTASSIUM CETYL PHOSPHATE; EDETATE DISODIUM; CETOSTEARYL ALCOHOL

Active ingredients

HYALURONATE SODIUM 1%

purpose

Slimming Hot Cream

uses

Apply hot jelly to the affected areas twice daily. It will be absorbed into the skin. The ingredients start breaking down the fat cells, leaving a supple and more toned skin.

warning

Avoid eyes and mucus membranes including ears, nose, mouth, genital, urethral, anus and other sensitive areas. Wash your hands after application. Please use a small amount first on a small area, leave and continue if you are comfortable to proceed. Discontinue use if irritation occurs. Do not use on the spots with injury, eczema, or dermatitis. Keep out of the reach of children.Weight loss, Relaxation and Massage, These Statements have not been evaluated by the food and drug administration. This product is not intended to diagnose, mitigate, treat, cure or prevent any disease.

Dosage and administration

For external use only.

Do not use

Avoid eyes and mucus membranes including ears, nose, mouth, genital, urethral, anus and other sensitive areas. Wash your hands after application. Please use a small amount first on a small area, leave and continue if you are comfortable to proceed. Discontinue use if irritation occurs. Do not use on the spots with injury, eczema, or dermatitis.

When using this product

Avoid eyes and mucus membranes including ears, nose, mouth, genital, urethral, anus and other sensitive areas. Do not use on the spots with injury, eczema, or dermatitis.

Stop use and ask a doctor if

Discontinue use if irritation occurs.

Keep out of reach of children.

Keep out of the reach of children.If swallowed, get medical help or contact a Poison Control Center right away.

Inactive ingredients

Water,Glycerin,Butylene Glycol,Cetearyl Alcohol,Ethylhexyl Palmitate, Caprylic/Capric Triglyceride,Isopropyl Myristate,Dimethicone,Potassium Cetyl Phosphate,Beta-Glucan,Sucrose Tristearate,Polyacrylamide,Phenoxyethanol, Vanillyl Butyl Ether, Hydroxyacetophenone,C13-14 Isoparaffin,Citric Acid,Parfum,Laureth-7,Disodium EDTA,Sodium Hyaluronate,Capsicum Annuum Extract,CI 15985,CI 19140